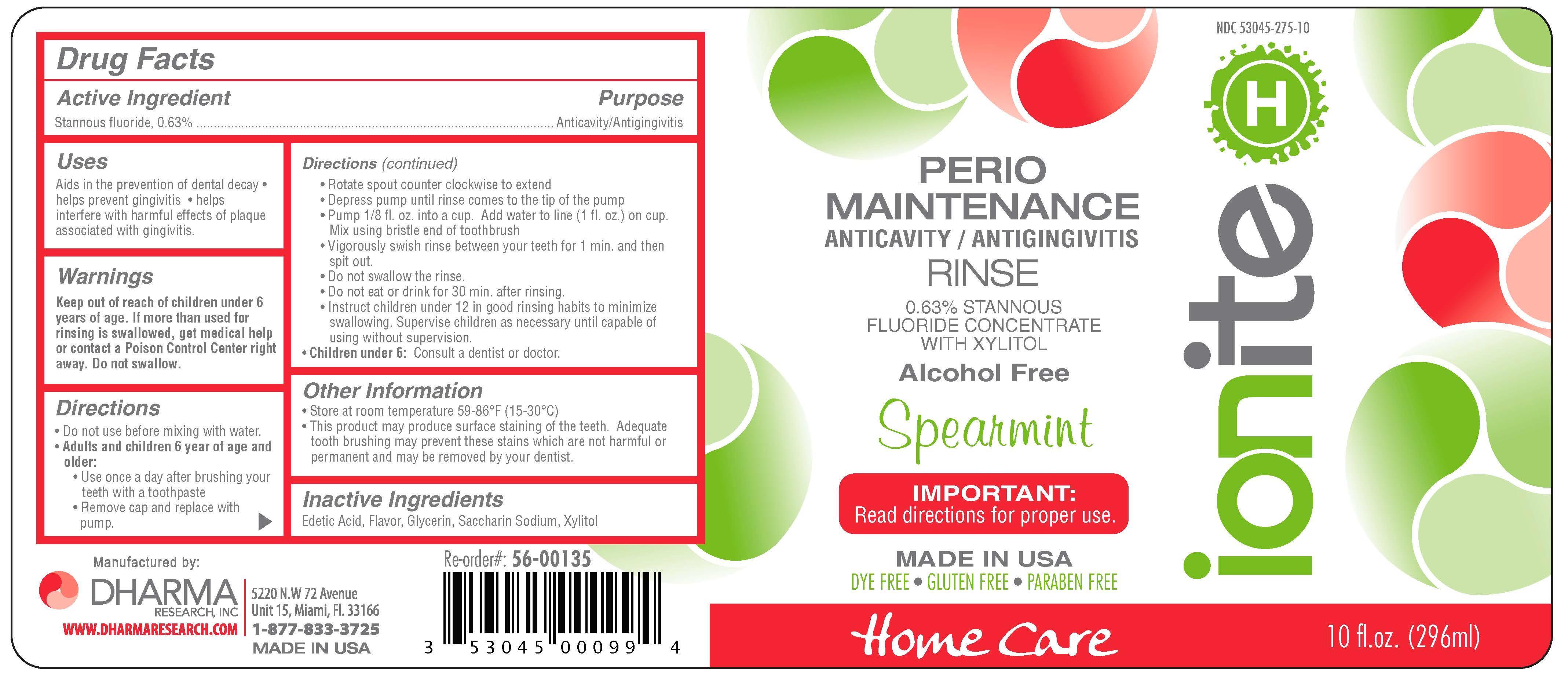 DRUG LABEL: Ionite H
NDC: 53045-275 | Form: MOUTHWASH
Manufacturer: Dharma Research, Inc.
Category: otc | Type: HUMAN OTC DRUG LABEL
Date: 20231011

ACTIVE INGREDIENTS: STANNOUS FLUORIDE 0.63 mg/100 mL
INACTIVE INGREDIENTS: EDETIC ACID; GLYCERIN; SACCHARIN SODIUM; XYLITOL

Active Ingredient

Stannous fluoride, 0.63%

Purpose

Anticavity/antigingivitis

Uses

- Aids in the prevention of dental decay

- Helps prevent gingivitis

- Helps interfere with harmful effects of plaque associated with gingivitis

Warnings

Keep out of reach of children under 6 years of age. If more than used for rinsing is swallowed, get medical help or contact a Poison Control center right away.

Do not swallow.

Directions

• Do not use before mixing with water
• Adults and children 6 years of age and older:
- Use once per day after brushing your teeth with toothpaste
- Remove cap and replace with pump
- Rotate spout counter clockwise to extend
- Depress pump until rinse comes to the tip of the pump
- Pump 1/8 fl. oz. into a cup.
- Add water to the line (1 fl. oz.) on cup.
- Mix using bristle end of toothbrush
- Vigorously swish rinse between your teeth for 1 min. and then spit out.
- Do not swallow the rinse
- Do not eat or drink for 30 min. after rinsing
- Instruct children under 12 in good rinsing habits to minimize swallowing.
- Supervise children as necessary until capable of using without supervision
• Children under 6: Consult a dentist or doctor

Other Information

- Store at room temperature 59 – 86°F (15 – 30°C).

- This product may produce surface staining of the teeth. Adequate tooth brushing may prevent these stains which are not harmful or permanent and may be removed by your dentist.

Inactive Ingredients

Edetic acid, Flavor, Glycerin, Saccharin Sodium, Xylitol

Manufactured by Dharma Research, Inc.

www.dharmaresearch.com

5220 N.W. 72 Avenue, Unit 15

Miami, FL 33166

1-877-833-3725

Reorder#: 56-00135

Ionite H

NDC 53045-275-10

PERIO MAINTENANCE ANTICAVITY/ANTIGINGIVITIS RINSE

0.63 Stannous Fluoride Concentrate with Xylitol

Alcohol Free

Spearmint

IMPORTANT: Read directions for proper use.

Made in USA

Dye Free Gluten Free Paraben Free

Home Care

10 fl. oz. (296 mL)